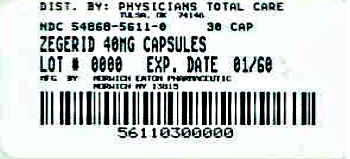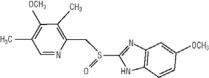 DRUG LABEL: Zegerid
NDC: 54868-5611 | Form: CAPSULE
Manufacturer: Physicians Total Care, Inc.
Category: prescription | Type: HUMAN PRESCRIPTION DRUG LABEL
Date: 20120501

ACTIVE INGREDIENTS: omeprazole 40 mg/1 1; sodium bicarbonate 1100 mg/1 1
INACTIVE INGREDIENTS: croscarmellose sodium; sodium stearyl fumarate

HIGHLIGHTS OF PRESCRIBING INFORMATION

These highlights do not include all the information needed to use ZEGERID safely and effectively. See full prescribing information for ZEGERID.
ZEGERID (omeprazole/sodium bicarbonate) Powder for Oral Suspension ZEGERID (omeprazole/sodium bicarbonate) Capsules
Initial U.S. Approval: 2004

RECENT MAJOR CHANGES

Warnings and Precautions, Hypomagnesemia (5.6) 05/2011

Warnings and Precautions, 11/2011

Diminished anti-platelet activity of clopidogrel (5.5)

Warnings and Precautions, 04/2012
Concomitant Use of Zegerid with Methotrexate (5.7)

1 INDICATIONS AND USAGE

ZEGERID is a proton pump inhibitor indicated for:

- Short-term treatment of active duodenal ulcer (1.1)
- Short-term treatment of active benign gastric ulcer (1.2)
- Treatment of gastroesophageal reflux disease (GERD) (1.3)
- Maintenance of healing of erosive esophagitis (1.4)
- Reduction of risk of upper GI bleeding in critically ill patients (1.5)

The safety and effectiveness of ZEGERID in pediatric patients (<18 years of age) have not been established. (8.4)

2 DOSAGE AND ADMINISTRATION

- Short-Term Treatment of Active Duodenal Ulcer: 20 mg once daily for 4 weeks (some patients may require an additional 4 weeks of therapy (14.1)) (2)
- Gastric Ulcer: 40 mg once daily for 4-8 weeks (2)
- Gastroesophageal Reflux Disease (GERD) (2)
  - Symptomatic GERD (with no esophageal erosions): 20 mg once daily for up to 4 weeks
  - Erosive Esophagitis: 20 mg once daily for 4-8 weeks
- Maintenance of Healing of Erosive Esophagitis: 20 mg once daily (2)
- Reduction of Risk of Upper Gastrointestinal Bleeding in Critically Ill Patients: (40mg oral suspension only) 40 mg initially followed by 40 mg 6-8 hours later and 40 mg daily thereafter for 14 days (2)

3 DOSAGE FORMS AND STRENGTHS

- ZEGERID is available as a capsule and as a powder for oral suspension in 20 mg and 40 mg strengths (3)

4 CONTRAINDICATIONS

- Known hypersensitivity to any components of the formulation (4)

5 WARNINGS AND PRECAUTIONS

- Concomitant Gastric Malignancy: Symptomatic response to therapy with ZEGERID does not preclude the presence of gastric malignancy (5.1)
- Atrophic Gastritis: Has been observed in gastric corpus biopsies from patients treated long-term with omeprazole (5.2)
- Buffer Content: contains sodium bicarbonate (5.3)
- Bone Fracture: Long-term and multiple daily dose PPI therapy may be associated with an increased risk for osteoporosis-related fractures of the hip, wrist, or spine. (5.4)
- Diminished anti-platelet activity of clopidogrel due to impaired CYP2C19 function by 80 mg omeprazole (5.5)
- Hypomagnesemia has been reported rarely with prolonged treatment with PPIs (5.6)

6 ADVERSE REACTIONS

Most common adverse reactions (incidence ≥ 2%) are:

Headache, abdominal pain, nausea, diarrhea, vomiting, and flatulence (6)

To report SUSPECTED ADVERSE REACTIONS, contact Santarus Inc. at 1-888-778-0887 or http://www.santarus.com/contact/, or FDA at 1-800-FDA-1088 or www.fda.gov/medwatch.

7 DRUG INTERACTIONS

- Drugs metabolized by cytochrome P450 (e.g., diazepam, warfarin, phenytoin, cyclosporine, disulfiram, benzodiazepines): ZEGERID can prolong their elimination. Monitor to determine the need for possible dose adjustments when taken with ZEGERID (7)
- Patients treated with proton pump inhibitors and warfarin concomitantly may need to be monitored for increases in INR and prothrombin time (7)
- Drugs for which gastric pH can affect bioavailability (e.g., ketoconazole, ampicillin esters, iron salts, and digoxin): ZEGERID may interfere with absorption due to inhibition of gastric acid secretion (7)
- Voriconazole: May increase plasma levels of omeprazole (7)
- ZEGERID may reduce plasma levels of atazanavir and nelfinavir (7)
- ZEGERID may increase serum levels of tacrolimus, voriconazole, saquinavir, and clarithromycin (7)
- Co-administration of clopidogrel with 80 mg omeprazole may reduce the pharmacological activity of clopidogrel if given concomitantly or if given 12 hours apart (7)
- Methotrexate: Zegerid may increase serum level of methotrexate (7.7)

8 USE IN SPECIFIC POPULATIONS

- Pregnancy: Based upon animal data, may cause fetal harm (8.1)
- The safety and effectiveness of ZEGERID in pediatric patients less than 18 years of age have not been established. (8.4)
- Hepatic Impairment: Consider dose reduction, particularly for maintenance of healing of erosive esophagitis (12.3)

FULL PRESCRIBING INFORMATION

1 INDICATIONS AND USAGE

1.1 Duodenal Ulcer

ZEGERID (omeprazole/sodium bicarbonate) is indicated for short-term treatment of active duodenal ulcer. Most patients heal within four weeks. Some patients may require an additional four weeks of therapy. [See Clinical Studies (14.1)]

1.2 Gastric Ulcer

ZEGERID is indicated for short-term treatment (4-8 weeks) of active benign gastric ulcer. [See Clinical Studies (14.2)]

1.3 Treatment of Gastroesophageal Reflux Disease (GERD)

Symptomatic GERD

ZEGERID is indicated for the treatment of heartburn and other symptoms associated with GERD. [See Clinical Studies (14.3)]

Erosive Esophagitis

ZEGERID is indicated for the short-term treatment (4-8 weeks) of erosive esophagitis which has been diagnosed by endoscopy.

The efficacy of ZEGERID used for longer than 8 weeks in these patients has not been established. If a patient does not respond to 8 weeks of treatment, it may be helpful to give up to an additional 4 weeks of treatment. If there is recurrence of erosive esophagitis or GERD symptoms (e.g., heartburn), additional 4-8 week courses of ZEGERID may be considered. [See Clinical Studies (14.3)]

1.4 Maintenance of Healing of Erosive Esophagitis

ZEGERID is indicated to maintain healing of erosive esophagitis. Controlled studies do not extend beyond 12 months. [See Clinical Studies (14.4)]

1.5 Reduction of Risk of Upper Gastrointestinal Bleeding in Critically Ill Patients (40mg oral suspension only)

ZEGERID Powder for Oral Suspension 40 mg/1680 mg is indicated for the reduction of risk of upper GI bleeding in critically ill patients. [See CLINICAL STUDIES, Reduction of Risk of Upper Gastrointestinal Bleeding in Critically Ill Patients (14.5)]

2 DOSAGE AND ADMINISTRATION

ZEGERID (omeprazole/sodium bicarbonate) is available as a capsule and as a powder for oral suspension in 20 mg and 40 mg strengths of omeprazole for adult use. Directions for use for each indication are summarized in Table 1. All recommended doses throughout the labeling are based upon omeprazole

Since both the 20 mg and 40 mg oral suspension packets contain the same amount of sodium bicarbonate (1680 mg), two packets of 20 mg are not equivalent to one packet of ZEGERID 40 mg; therefore, two 20 mg packets of ZEGERID should not be substituted for one packet of ZEGERID 40 mg.

Since both the 20 mg and 40 mg capsules contain the same amount of sodium bicarbonate (1100 mg), two capsules of 20 mg are not equivalent to one capsule of ZEGERID 40 mg; therefore, two 20 mg capsules of ZEGERID should not be substituted for one capsule of ZEGERID 40 mg.

ZEGERID should be taken on an empty stomach at least one hour before a meal.

For patients receiving continuous Nasogastric (NG)/ Orogastric (OG) tube feeding, enteral feeding should be suspended approximately 3 hours before and 1 hour after administration of ZEGERID Powder for Oral Suspension.

Table 1: Recommended Doses of ZEGERID by Indication for Adults 18 Years and Older
Indication | Recommended Dose | Frequency
Short-Term Treatment of Active Duodenal Ulcer | 20 mg | Once daily for 4 weeks*,+
Benign Gastric Ulcer | 40 mg | Once daily for 4-8 weeks **,+
Gastroesophageal Reflux Disease (GERD)
Symptomatic GERD (with no esophageal erosions) | 20 mg | Once daily for up to 4 weeks^+
Erosive Esophagitis | 20 mg | Once daily for 4-8 weeks^+
Maintenance of Healing of Erosive Esophagitis | 20 mg | Once daily**
Reduction of Risk of Upper Gastrointestinal Bleeding in Critically Ill Patients (40 mg oral suspension only) | 40 mg | 40 mg initially followed by 40 mg 6-8 hours later and 40 mg daily thereafter for 14 days**
* Most patients heal within 4 weeks. Some patients may require an additional 4 weeks of therapy. [See Clinical Studies (14.1)]
** For additional information, [See Clinical Studies (14)]
^+ For additional information, [See Indications and Usage (1)]

Special Populations

Hepatic Insufficiency

Consider dose reduction, particularly for maintenance of healing of erosive esophagitis. [See Clinical Pharmacology (12.3)]

Administration of Capsules

ZEGERID Capsules should be swallowed intact with water. DO NOT USE OTHER LIQUIDS. DO NOT OPEN CAPSULE AND SPRINKLE CONTENTS INTO FOOD.

Preparation and Administration of Suspension

Directions for use: Empty packet contents into a small cup containing 1-2 tablespoons of water. DO NOT USE OTHER LIQUIDS OR FOODS. Stir well and drink immediately. Refill cup with water and drink.

If ZEGERID is to be administered through a nasogastric (NG) or orogastric (OG) tube, the suspension should be constituted with approximately 20 mL of water. DO NOT USE OTHER LIQUIDS OR FOODS. Stir well and administer immediately. An appropriately-sized syringe should be used to instill the suspension in the tube. The suspension should be washed through the tube with 20 mL of water.

Use with clopidogrel

Avoid concomitant use of clopidogrel and omeprazole. Coadministration of clopidogrel with 80 mg omeprazole, a proton pump inhibitor that is an inhibitor of CYP2C19, reduces the pharmacological activity of clopidogrel if given concomitantly or if given 12 hours apart [see Warnings and Precautions (5.6) and Drug Interactions (7)].

3 DOSAGE FORMS AND STRENGTHS

ZEGERID 20-mg Capsules: Each opaque, hard gelatin, white capsule, imprinted with the Santarus logo and “20”, contains 20 mg omeprazole and 1100 mg sodium bicarbonate.

ZEGERID 40-mg Capsules: Each opaque, hard gelatin, colored dark blue and white capsule, imprinted with the Santarus logo and “40”, contains 40 mg omeprazole and 1100 mg sodium bicarbonate.

ZEGERID Powder for Oral Suspension is a white, flavored powder packaged in unit-dose packets. Each packet contains either 20 mg or 40 mg omeprazole and 1680 mg sodium bicarbonate.

4 CONTRAINDICATIONS

ZEGERID is contraindicated in patients with known hypersensitivity to any components of the formulation. Hypersensitivity reactions may include anaphylaxis, anaphylactic shock, angioedema, bronchospasm, interstitial nephritis, and urticaria.

5 WARNINGS AND PRECAUTIONS

5.1 Concomitant Gastric Malignancy

Symptomatic response to therapy with omeprazole does not preclude the presence of gastric malignancy.

5.2 Atrophic gastritis

Atrophic gastritis has been noted occasionally in gastric corpus biopsies from patients treated long-term with omeprazole.

5.3 Buffer Content

Each ZEGERID Capsule contains 1100 mg (13 mEq) of sodium bicarbonate. The total content of sodium in each capsule is 304 mg.

Each packet of ZEGERID Powder for Oral Suspension contains 1680 mg (20 mEq) of sodium bicarbonate (equivalent to 460 mg of Na+).

The sodium content of ZEGERID products should be taken into consideration when administering to patients on a sodium restricted diet.

Because ZEGERID products contain sodium bicarbonate, they should be used with caution in patients with Bartter's syndrome, hypokalemia, hypocalcemia, and problems with acid-base balance. Long-term administration of bicarbonate with calcium or milk can cause milk-alkali syndrome.

Chronic use of sodium bicarbonate may lead to systemic alkalosis and increased sodium intake can produce edema and weight increase.

5.4 Bone Fracture

Several published observational studies suggest that proton pump inhibitor (PPI) therapy may be associated with an increased risk for osteoporosis-related fractures of the hip, wrist, or spine. The risk of fracture was increased in patients who received high-dose, defined as multiple daily doses, and long-term PPI therapy (a year or longer). Patients should use the lowest dose and shortest duration of PPI therapy appropriate to the condition being treated. Patients at risk for osteoporosis-related fractures should be managed according to the established treatment guidelines. [See Dosage and Administration (2) and Adverse Reactions (6.2)]

5.5 Diminished Anti-platelet Activity of clopidogrel due to Impaired CYP2C19 Function by Omeprazole

Clopidogrel is a prodrug. Inhibition of platelet aggregation by clopidogrel is entirely due to an active metabolite. The metabolism of clopidogrel to its active metabolite can be impaired by use with concomitant medications, such as omeprazole, that interfere with CYP2C19 activity. Avoid concomitant use of clopidogrel and omeprazole. Co-administration of clopidogrel with 80 mg omeprazole, a proton pump inhibitor that is an inhibitor of CYP2C19, reduces the pharmacological activity of clopidogrel if given concomitantly or if given 12 hours apart [see Drug Interactions (7)].

5.6 Hypomagnesemia

Hypomagnesemia, symptomatic and asymptomatic, has been reported rarely in patients treated with PPIs for at least three months, in most cases after a year of therapy. Serious adverse events include tetany, arrhythmias, and seizures. In most patients, treatment of hypomagnesemia required magnesium replacement and discontinuation of the PPI.

For patients expected to be on prolonged treatment or who take PPIs with medications such as digoxin or drugs that may cause hypomagnesemia (e.g., diuretics), health care professionals may consider monitoring magnesium levels prior to initiation of PPI treatment and periodically. [See Adverse Reactions (6.2)]

5.7 Concomitant use of Zegerid with Methotrexate

Literature suggests that concomitant use of PPIs with methotrexate (primarily at high dose; see methotrexate prescribing information) may elevate and prolong serum levels of methotrexate and/or its metabolite, possibly leading to methotrexate toxicities. In high-dose methotrexate administration, a temporary withdrawal of the PPI may be considered in some patients. [See Drug Interactions (7.7)

6 ADVERSE REACTIONS

6.1 Clinical Trials Experience

Because clinical trials are conducted under widely varying conditions, adverse reaction rates observed in the clinical trials of a drug cannot be directly compared to rates in the clinical trials of another drug and may not reflect the rates observed in clinical practice.

In the U.S. clinical trial population of 465 patients, the adverse reactions summarized in Table 2 were reported to occur in 1% or more of patients on therapy with omeprazole. Numbers in parentheses indicate percentages of the adverse reactions considered by investigators as possibly, probably or definitely related to the drug.

Table 2: Adverse Reactions Occurring In 1% or More of Patients on Omeprazole Therapy
 | Omeprazole (n = 465) | Placebo (n = 64) | Ranitidine (n = 195)
Headache | 6.9 (2.4) | 6.3 | 7.7 (2.6)
Diarrhea | 3.0 (1.9) | 3.1 (1.6) | 2.1 (0.5)
Abdominal Pain | 2.4 (0.4) | 3.1 | 2.1
Nausea | 2.2 (0.9) | 3.1 | 4.1 (0.5)
URI | 1.9 | 1.6 | 2.6
Dizziness | 1.5 (0.6) | 0.0 | 2.6 (1.0)
Vomiting | 1.5 (0.4) | 4.7 | 1.5 (0.5)
Rash | 1.5 (1.1) | 0.0 | 0.0
Constipation | 1.1 (0.9) | 0.0 | 0.0
Cough | 1.1 | 0.0 | 1.5
Asthenia | 1.1 (0.2) | 1.6 (1.6) | 1.5 (1.0)
Back Pain | 1.1 | 0.0 | 0.5

Table 3 summarizes the adverse reactions that occurred in 1% or more of omeprazole-treated patients from international double-blind, and open-label clinical trials in which 2,631 patients and subjects received omeprazole.

Table 3: Incidence of Adverse Reactions ≥ 1% Causal Relationship not Assessed
 | Omeprazole (n = 2631) | Placebo (n = 120)
Body as a Whole, site unspecified
Abdominal pain | 5.2 | 3.3
Asthenia | 1.3 | 0.8
Digestive System
Constipation | 1.5 | 0.8
Diarrhea | 3.7 | 2.5
Flatulence | 2.7 | 5.8
Nausea | 4.0 | 6.7
Vomiting | 3.2 | 10.0
Acid regurgitation | 1.9 | 3.3
Nervous System/Psychiatric
Headache | 2.9 | 2.5

A controlled clinical trial was conducted in 359 critically ill patients, comparing ZEGERID 40 mg/1680 mg suspension once daily to I.V. cimetidine 1200 mg/day for up to 14 days. The incidence and total number of AEs experienced by ≥ 3% of patients in either group are presented in Table 4 by body system and preferred term.

Table 4: Number (%) of Critically Ill Patients with Frequently Occurring (≥ 3%) Adverse Events by Body System and Preferred Term
 | ZEGERID® (N=178) | Cimetidine (N=181)
MedDRA Body System Preferred Term | All AEs n (%) | All AEs n (%)
BLOOD AND LYMPHATIC SYSTEM DISORDERS
Anemia NOS | 14 (7.9) | 14 (7.7)
Anemia NOS Aggravated | 4 (2.2) | 7 (3.9)
Thrombocytopenia | 18 (10.1) | 11 (6.1)
CARDIAC DISORDERS
Atrial Fibrillation | 11 (6.2) | 7 (3.9)
Bradycardia NOS | 7 (3.9) | 5 (2.8)
Supraventricular Tachycardia | 6 (3.4) | 2 (1.1)
Tachycardia NOS | 6 (3.4) | 6 (3.3)
Ventricular Tachycardia | 8 (4.5) | 6 (3.3)
GASTROINTESTINAL DISORDERS *
Constipation | 8 (4.5) | 8 (4.4)
Diarrhea NOS | 7 (3.9) | 15 (8.3)
Gastric Hypomotility | 3 (1.7) | 6 (3.3)
GENERAL DISORDERS AND ADMINISTRATION SITE CONDITIONS
Hyperpyrexia | 8 (4.5) | 3 (1.7)
Edema NOS | 5 (2.8) | 11 (6.1)
Pyrexia | 36 (20.2) | 29 (16.0)
INFECTIONS AND INFESTATIONS
Candidal Infection NOS | 3 (1.7) | 7 (3.9)
Oral Candidiasis | 7 (3.9) | 1 (0.6)
Sepsis NOS | 9 (5.1) | 9 (5.0)
Urinary Tract Infection NOS | 4 (2.2) | 6 (3.3)
INVESTIGATIONS
Liver Function Tests NOS Abnormal | 3 (1.7) | 6 (3.3)
METABOLISM AND NUTRITION DISORDERS
Fluid Overload | 9 (5.1) | 14 (7.7)
Hyperglycaemia NOS | 19 (10.7) | 21 (11.6)
Hyperkalaemia | 4 (2.2) | 6 (3.3)
Hypernatraemia | 3 (1.7) | 9 (5.0)
Hypocalcaemia | 11 (6.2) | 10 (5.5)
Hypoglycaemia NOS | 6 (3.4) | 8 (4.4)
Hypokalaemia | 22 (12.4) | 24 (13.3)
Hypomagnesaemia | 18 (10.1) | 18 (9.9)
Hyponatraemia | 7 (3.9) | 5 (2.8)
Hypophosphataemia | 11 (6.2) | 7 (3.9)
PSYCHIATRIC DISORDERS
Agitation | 6 (3.4) | 16 (8.8)
RESPIRATORY, THORACIC AND MEDIASTINAL DISORDERS
Acute Respiratory Distress Syndrome | 6 (3.4) | 7 (3.9)
Nosocomial Pneumonia | 20 (11.2) | 17 (9.4)
Pneumothorax NOS | 1 (0.6) | 8 (4.4)
Respiratory Failure | 3 (1.7) | 6 (3.3)
SKIN AND SUBCUTANEOUS TISSUE DISORDERS
Decubitus Ulcer | 6 (3.4) | 5 (2.8)
Rash NOS | 10 (5.6) | 11 (6.1)
VASCULAR DISORDERS
Hypertension NOS | 14 (7.9) | 6 (3.3)
Hypotension NOS | 17 (9.6) | 12 (6.6)
* Clinically significant upper gastrointestinal bleeding was considered a serious adverse event but it is not included in this table.
NOS = Not otherwise specified.

6.2 Postmarketing Experience

The following adverse reactions have been identified during post-approval use of omeprazole. Because these reactions are voluntarily reported from a population of uncertain size, it is not always possible to reliably estimate their actual frequency or establish a causal relationship to drug exposure.

Body as a Whole: Hypersensitivity reactions, including anaphylaxis, anaphylactic shock, angioedema, bronchospasm, interstitial nephritis, urticaria (see also Skin below), fever, pain, fatigue, malaise.

Cardiovascular: Chest pain or angina, tachycardia, bradycardia, palpitation, elevated blood pressure, and peripheral edema.

Gastrointestinal: Pancreatitis (some fatal), anorexia, irritable colon, flatulence, fecal discoloration, esophageal candidiasis, mucosal atrophy of the tongue, dry mouth, stomatitis and abdominal swelling. During treatment with omeprazole, gastric fundic gland polyps have been noted rarely. These polyps are benign and appear to be reversible when treatment is discontinued. Gastroduodenal carcinoids have been reported in patients with Zollinger-Ellison syndrome on long-term treatment with omeprazole. This finding is believed to be a manifestation of the underlying condition, which is known to be associated with such tumors.

Hepatic: Mild and, rarely, marked elevations of liver function tests [ALT (SGPT), AST (SGOT), γ-glutamyl transpeptidase, alkaline phosphatase, and bilirubin (jaundice)]. In rare instances, overt liver disease has occurred, including hepatocellular, cholestatic, or mixed hepatitis, liver necrosis (some fatal), hepatic failure (some fatal), and hepatic encephalopathy.

Metabolism and Nutritional Disorders: Hyponatremia, hypoglycemia, hypomagnesemia, and weight gain.

Musculoskeletal: Muscle cramps, myalgia, muscle weakness, joint pain, bone fracture, and leg pain.

Nervous System/Psychiatric: Psychic disturbances including depression, agitation, aggression, hallucinations, confusion, insomnia, nervousness, tremors, apathy, somnolence, anxiety, dream abnormalities; vertigo; paresthesia; and hemifacial dysesthesia.

Respiratory: Epistaxis, pharyngeal pain.

Skin: Severe generalized skin reactions including toxic epidermal necrolysis (TEN; some fatal), Stevens-Johnson syndrome, and erythema multiforme (some severe); purpura and/or petechiae (some with rechallenge); skin inflammation, urticaria, angioedema, pruritus, photosensitivity, alopecia, dry skin, and hyperhidrosis.

Special Senses: Tinnitus, taste perversion.

Ocular: Blurred vision, ocular irritation, dry eye syndrome, optic atrophy, anterior ischemic optic neuropathy, optic neuritis and double vision.

Urogenital: Interstitial nephritis (some with positive rechallenge), urinary tract infection, microscopic pyuria, urinary frequency, elevated serum creatinine, proteinuria, hematuria, glycosuria, testicular pain, and gynecomastia.

Hematologic: Rare instances of pancytopenia, agranulocytosis (some fatal), thrombocytopenia, neutropenia, leukopenia, anemia, leucocytosis, and hemolytic anemia have been reported.

The incidence of clinical adverse experiences in patients greater than 65 years of age was similar to that in patients 65 years of age or less.

Additional adverse reactions that could be caused by sodium bicarbonate include metabolic alkalosis, seizures, and tetany.

7 DRUG INTERACTIONS

7.1 Drugs for which gastric pH can affect bioavailability

Because of its inhibition of gastric acid secretion, it is theoretically possible that omeprazole may interfere with absorption of drugs where gastric pH is an important determinant of their bioavailability (e.g., ketoconazole, ampicillin esters, iron salts, and digoxin). In the clinical efficacy trials, antacids were used concomitantly with the administration of omeprazole.

7.2 Drugs metabolized by cytochrome P450 (CYP)

Omeprazole can prolong the elimination of diazepam, warfarin and phenytoin, drugs that are metabolized by oxidation in the liver. There have been reports of increased INR and prothrombin time in patients receiving proton pump inhibitors, including omeprazole, and warfarin concomitantly. Increases in INR and prothrombin time may lead to abnormal bleeding and even death. Patients treated with proton pump inhibitors and warfarin may need to be monitored for increases in INR and prothrombin time.

Although in normal subjects no interaction with theophylline or propranolol was found, there have been clinical reports of interaction with other drugs metabolized via the cytochrome P-450 system (e.g., cyclosporine, disulfiram, benzodiazepines). Patients should be monitored to determine if it is necessary to adjust the dosage of these drugs when taken concomitantly with ZEGERID.

Concomitant administration of omeprazole and voriconazole (a combined inhibitor of CYP2C19 and CYP3A4) resulted in more than doubling of the omeprazole exposure. Dose adjustment of omeprazole is not normally required.. When voriconazole (400 mg every 12 hours for one day, then 200 mg for 6 days) was given with omeprazole (40 mg once daily for 7 days) to healthy subjects, it significantly increased the steady-state Cmax and AUC0-24 of omeprazole, an average of 2 times (90% CI: 1.8, 2.6) and 4 times (90% CI: 3.3, 4.4) respectively as compared to when omeprazole was given without voriconazole.

7.3 Antiretroviral Agents

Concomitant administration of atazanavir and proton pump inhibitors is not recommended. Co-administration of atazanavir with proton pump inhibitors is expected to substantially decrease atazanavir plasma concentrations and thereby reduce its therapeutic effect.

Omeprazole has been reported to interact with some antiretroviral drugs. The clinical importance and the mechanisms behind these interactions are not always known. Increased gastric pH during omeprazole treatment may change the absorption of the antiretroviral drug. Other possible interaction mechanisms are via CYP2C19. For some antiretroviral drugs, such as atazanavir and nelfinavir, decreased serum levels have been reported when given together with omeprazole. Following multiple doses of nelfinavir (1250 mg, twice daily) and omeprazole (40 mg, daily), AUC was decreased by 36% and 92%, Cmax by 37% and 89% and Cmin by 39% and 75% respectively for nelfinavir and M8. Following multiple doses of atazanavir (400 mg, daily) and omeprazole (40 mg, daily, 2 hours before atazanavir), AUC was decreased by 94%, Cmax by 96%, and Cmin by 95%. Concomitant administration with omeprazole and drugs such as atazanavir and nelfinavir is therefore not recommended. For other antiretroviral drugs, such as saquinavir, elevated serum levels have been reported with an increase in AUC by 82%, in Cmax by 75% and in Cmin by 106% following multiple dosing of saquinavir/ritonavir (1000/100 mg) twice daily for 15 days with omeprazole 40 mg daily co-administered days 11 to 15. Dose reduction of saquinavir should be considered from the safety perspective for individual patients. There are also some antiretroviral drugs of which unchanged serum levels have been reported when given with omeprazole.

7.4 Antimicrobials

Omeprazole 40 mg daily was given in combination with clarithromycin 500 mg every 8 hours to healthy adult male subjects. The steady state plasma concentrations of omeprazole were increased (Cmax, AUC0-24, and T1/2 increases of 30%, 89% and 34% respectively) by the concomitant administration of clarithromycin. The observed increases in omeprazole plasma concentration were associated with the following pharmacological effects. The mean 24-hour gastric pH value was 5.2 when omeprazole was administered alone and 5.7 when co-administered with clarithromycin.

The plasma levels of clarithromycin and 14-hydroxyclarithromycin were increased by the concomitant administration of omeprazole. For clarithromycin, the mean Cmax was 10% greater, the mean Cmin was 27% greater, and the mean AUC0-8 was 15% greater when clarithromycin was administered with omeprazole than when clarithromycin was administered alone. Similar results were seen for 14-hydroxyclarithromycin, the mean Cmax was 45% greater, the mean Cmin was 57% greater, and the mean AUC0-8 was 45% greater. Clarithromycin concentrations in the gastric tissue and mucus were also increased by concomitant administration of omeprazole.

Table 5: Clarithromycin Tissue Concentrations 2 hours after Dose^1
Tissue | Clarithromycin | Clarithromycin + Omeprazole
Antrum | 10.48 ± 2.01 (n = 5) | 19.96 ± 4.71 (n = 5)
Fundus | 20.81 ± 7.64 (n = 5) | 24.25 ± 6.37 (n = 5)
Mucus | 4.15 ± 7.74 (n = 4) | 39.29 ± 32.79 (n = 4)
 | ^1Mean ± (μg/g)

7.5 Clopidogrel

Omeprazole is an inhibitor of CYP2C19 enzyme. Clopidogrel is metabolized to its active metabolite in part by CYP2C19. Concomitant use of omeprazole 80 mg results in reduced plasma concentrations of the active metabolite of clopidogrel and a reduction in platelet inhibition [see Warnings and Precautions (5.6)].

In a crossover clinical study, 72 healthy subjects were administered clopidogrel (300 mg loading dose followed by 75 mg per day) alone and with omeprazole (80 mg at the same time as clopidogrel) for 5 days. The exposure to the active metabolite of clopidogrel was decreased by 46% (Day 1) and 42% (Day 5) when clopidogrel and omeprazole were administered together. The active metabolite of clopidogrel selectively and irreversibly inhibits the binding of adenosine diphosphate (ADP) to its platelet P2Y12 receptor, thereby inhibiting platelet aggregation. The mean inhibition of platelet aggregation at 5 mcM ADP was diminished by 39% (Day 1) and 21% (Day 5) when clopidogrel and omeprazole were administered together.

In another study, 72 healthy subjects were given the same doses of clopidogrel and 80 mg omeprazole but the drugs were administered12 hours apart; the results were similar, indicating that administering clopidogrel and omeprazole at different times does not prevent their interaction [see Warnings and Precautions (5.6)].

There are no adequate combination studies of a lower dose of omeprazole or a higher dose of clopidogrel in comparison with the approved dose of clopidogrel.

7.6 Tacrolimus

Concomitant administration of omeprazole and tacrolimus may increase the serum levels of tacrolimus.

7.7 Methotrexate

Case reports, published population pharmacokinetic studies, and retrospective analyses suggest that concomitant administration of PPIs and methotrexate (primarily at high dose; see methotrexate prescribing information) may elevate and prolong serum levels of methotrexate and/or its metabolite hydroxymethotrexate. However, no formal drug interaction studies of methotrexate with PPIs have been conducted. [see Warnings and Precautions (5.7).

8 USE IN SPECIFIC POPULATIONS

8.1 Pregnancy

Pregnancy Category C

There are no adequate and well-controlled studies on the use of omeprazole in pregnant women. The vast majority of reported experience with omeprazole during human pregnancy is first trimester exposure and the duration of use is rarely specified, eg, intermittent versus chronic. An expert review of published data on experiences with omeprazole use during pregnancy by TERIS – the Teratogen Information System – concluded that therapeutic doses during pregnancy are unlikely to pose a substantial teratogenic risk (the quantity and quality of data were assessed as fair).^1

Three epidemiological studies compared the frequency of congenital abnormalities among infants born to women who used omeprazole during pregnancy to the frequency of abnormalities among infants of women exposed to H2-receptor antagonists or other controls. A population-based prospective cohort epidemiological study from the Swedish Medical Birth Registry, covering approximately 99% of pregnancies, reported on 955 infants (824 exposed during the first trimester with 39 of these exposed beyond first trimester, and 131 exposed after the first trimester) whose mothers used omeprazole during pregnancy.^2 In utero exposure to omeprazole was not associated with increased risk of any malformation (odds ratio 0.82, 95% CI 0.50-1.34), low birth weight or low Apgar score. The number of infants born with ventricular septal defects and the number of stillborn infants was slightly higher in the omeprazole exposed infants than the expected number in the normal population. The author concluded that both effects may be random.

A retrospective cohort study reported on 689 pregnant women exposed to either H2-blockers or omeprazole in the first trimester (134 exposed to omeprazole).^3 The overall malformation rate was 4.4% (95% CI 3.6-5.3) and the malformation rate for first trimester exposure to omeprazole was 3.6% (95% CI 1.5-8.1). The relative risk of malformations associated with first trimester exposure to omeprazole compared with nonexposed women was 0.9 (95% CI 0.3-2.2). The study could effectively rule out a relative risk greater than 2.5 for all malformations. Rates of preterm delivery or growth retardation did not differ between the groups.

A controlled prospective observational study followed 113 women exposed to omeprazole during pregnancy (89% first trimester exposures).^4 The reported rates of major congenital malformations was 4% for the omeprazole group, 2% for controls exposed to nonteratogens, and 2.8% in disease-paired controls (background incidence of major malformations 1-5%). Rates of spontaneous and elective abortions, preterm deliveries, gestational age at delivery, and mean birth weight did not differ between the groups. The sample size in this study has 80% power to detect a 5-fold increase in the rate of major malformation.

Several studies have reported no apparent adverse short term effects on the infant when single dose oral or intravenous omeprazole was administered to over 200 pregnant women as premedication for cesarean section under general anesthesia.

Reproduction studies conducted with omeprazole in rats at oral doses up to 28 times the human dose of 40 mg/day (based on body surface area) and in rabbits at doses up to 28 times the human dose (based on body surface area) did not show any evidence of teratogenicity. In pregnant rabbits, omeprazole at doses about 2.8 to 28 times the human dose of 40 mg/day, (based on body surface area) produced dose-related increases in embryo-lethality, fetal resorptions, and pregnancy loss. In rats treated with omeprazole at doses about 2.8 to 28 times the human dose (based on body surface area), dose-related embryo/fetal toxicity and postnatal developmental toxicity occurred in offspring. [See Animal Toxicology and/or Pharmacology (13.2)].

There are no adequate and well-controlled studies in pregnant women. Because animal studies and studies in humans cannot rule out the possibility of harm, ZEGERID should be used during pregnancy only if the potential benefit to pregnant women justifies the potential risk to the fetus.

8.3 Nursing Mothers

Omeprazole concentrations have been measured in breast milk of a woman following oral administration of 20 mg. The peak concentration of omeprazole in breast milk was less than 7% of the peak serum concentration. The concentration will correspond to 0.004 mg of omeprazole in 200 mL of milk. Because omeprazole is excreted in human milk, because of the potential for serious adverse reactions in nursing infants from omeprazole, and because of the potential for tumorigenicity shown for omeprazole in rat carcinogenicity studies, a decision should be made to discontinue nursing or to discontinue the drug, taking into account the importance of the drug to the mother. In addition, sodium bicarbonate should be used with caution in nursing mothers.

8.4 Pediatric Use

Safety and effectiveness of ZEGERID have not been established in pediatric patients less than 18 years of age.

8.5 Geriatric Use

Omeprazole was administered to over 2000 elderly individuals (≥ 65 years of age) in clinical trials in the U.S. and Europe. There were no differences in safety and effectiveness between the elderly and younger subjects. Other reported clinical experience has not identified differences in response between the elderly and younger subjects, but greater sensitivity of some older individuals cannot be ruled out.

Pharmacokinetic studies with buffered omeprazole have shown the elimination rate was somewhat decreased in the elderly and bioavailability was increased. The plasma clearance of omeprazole was 250 mL/min (about half that of young subjects). The plasma half-life averaged one hour, about twice that in nonelderly, healthy subjects taking ZEGERID. However, no dosage adjustment is necessary in the elderly. [See Clinical Pharmacology (12.3)]

8.6 Hepatic Impairment

Consider dose reduction, particularly for maintenance of healing of erosive esophagitis. [See Clinical Pharmacology (12.3)]

8.7 Renal Impairment

No dose reduction is necessary. [See Clinical Pharmacology (12.3)]

8.8 Asian Population

Recommend dose reduction, particularly for maintenance of healing of erosive esophagitis. [See Clinical Pharmacology (12.3)]

10 OVERDOSAGE

Reports have been received of overdosage with omeprazole in humans. Doses ranged up to 2400 mg (120 times the usual recommended clinical dose). Manifestations were variable, but included confusion, drowsiness, blurred vision, tachycardia, nausea, vomiting, diaphoresis, flushing, headache, dry mouth, and other adverse reactions similar to those seen in normal clinical experience. [See Adverse Reactions (6)] Symptoms were transient, and no serious clinical outcome has been reported when omeprazole was taken alone. No specific antidote for omeprazole overdosage is known. Omeprazole is extensively protein bound and is, therefore, not readily dialyzable. In the event of overdosage, treatment should be symptomatic and supportive.

As with the management of any overdose, the possibility of multiple drug ingestion should be considered. For current information on treatment of any drug overdose, a certified Regional Poison Control Center should be contacted. Telephone numbers are listed in the Physicians' Desk Reference (PDR) or local telephone book.

Single oral doses of omeprazole at 1350, 1339, and 1200 mg/kg were lethal to mice, rats, and dogs, respectively. Animals given these doses showed sedation, ptosis, tremors, convulsions, and decreased activity, body temperature, and respiratory rate and increased depth of respiration.

In addition, a sodium bicarbonate overdose may cause hypocalcemia, hypokalemia, hypernatremia, and seizures.

11 DESCRIPTION

ZEGERID® (omeprazole/sodium bicarbonate) is a combination of omeprazole, a proton-pump inhibitor, and sodium bicarbonate, an antacid. Omeprazole is a substituted benzimidazole, 5-methoxy-2-[[(4-methoxy-3,5-dimethyl-2-pyridinyl)methyl]sulfinyl]-1H-benzimidazole, a racemic mixture of two enantiomers that inhibits gastric acid secretion. Its empirical formula is C17H19N3O3S, with a molecular weight of 345.42. The structural formula is:

Omeprazole is a white to off-white crystalline powder which melts with decomposition at about 155°C. It is a weak base, freely soluble in ethanol and methanol, and slightly soluble in acetone and isopropanol and very slightly soluble in water. The stability of omeprazole is a function of pH; it is rapidly degraded in acid media, but has acceptable stability under alkaline conditions.

ZEGERID is supplied as immediate-release capsules and unit-dose packets as powder for oral suspension. Each capsule contains either 40 mg or 20 mg of omeprazole and 1100 mg of sodium bicarbonate with the following excipients: croscarmellose sodium and sodium stearyl fumarate. Packets of powder for oral suspension contain either 40 mg or 20 mg of omeprazole and 1680 mg of sodium bicarbonate with the following excipients: xylitol, sucrose, sucralose, xanthan gum, and flavorings.

12 CLINICAL PHARMACOLOGY

12.1 Mechanism of Action

Omeprazole belongs to a class of antisecretory compounds, the substituted benzimidazoles, that do not exhibit anticholinergic or H2 histamine antagonistic properties, but that suppress gastric acid secretion by specific inhibition of the H+/K+ ATPase enzyme system at the secretory surface of the gastric parietal cell. Because this enzyme system is regarded as the acid (proton) pump within the gastric mucosa, omeprazole has been characterized as a gastric acid-pump inhibitor, in that it blocks the final step of acid production. This effect is dose related and leads to inhibition of both basal and stimulated acid secretion irrespective of the stimulus. Animal studies indicate that after rapid disappearance from plasma, omeprazole can be found within the gastric mucosa for a day or more.

Omeprazole is acid labile and thus rapidly degraded by gastric acid. ZEGERID Capsules and Powder for Oral Suspension are immediate-release formulations that contain sodium bicarbonate which raises the gastric pH and thus protects omeprazole from acid degradation.

12.2 Pharmacodynamics

Antisecretory Activity

Results from a PK/PD study of the antisecretory effect of repeated once-daily dosing of 40 mg and 20 mg of ZEGERID Oral Suspension in healthy subjects are shown in Table 6 below.

Table 6: Effect of ZEGERID Oral Suspension on Intragastric pH, Day 7
 | Omeprazole/Sodium Bicarbonate
Parameter | 40 mg/1680 mg (n = 24) | 20 mg/1680 mg (n = 28)
% Decrease from Baseline for Integrated Gastric Acidity (mmol·hr/L) | 84% | 82%
Coefficient of variation | 20% | 24%
% Time Gastric pH > 4* (Hours) * | 77% (18.6 h) | 51% (12.2 h)
Coefficient of variation | 27% | 43%
Median pH | 5.2 | 4.2
Coefficient of variation | 17% | 37%
Note: Values represent medians. All parameters were measured over a 24-hour period.
* p < 0.05 20 mg vs. 40 mg

Results from a separate PK/PD study of antisecretory effect on repeated once-daily dosing of 40 mg/1100 mg and 20 mg/1100 mg of ZEGERID Capsules in healthy subjects show similar effects in general on the above three PD parameters as those for ZEGERID 40 mg/1680 mg and 20 mg/1680 mg Oral Suspension, respectively.

The antisecretory effect lasts longer than would be expected from the very short (1 hour) plasma half-life, apparently due to irreversible binding to the parietal H+/K+ ATPase enzyme.

Enterochromaffin-like (ECL) Cell Effects

In 24-month carcinogenicity studies in rats, a dose-related significant increase in gastric carcinoid tumors and ECL cell hyperplasia was observed in both male and female animals [See Nonclinical Toxicology (13.1)]. Carcinoid tumors have also been observed in rats subjected to fundectomy or long-term treatment with other proton pump inhibitors or high doses of H2-receptor antagonists. Human gastric biopsy specimens have been obtained from more than 3000 patients treated with omeprazole in long-term clinical trials. The incidence of ECL cell hyperplasia in these studies increased with time; however, no case of ECL cell carcinoids, dysplasia, or neoplasia has been found in these patients. These studies are of insufficient duration and size to rule out the possible influence of long-term administration of omeprazole on the development of any premalignant or malignant conditions.

Serum Gastrin Effects

In studies involving more than 200 patients, serum gastrin levels increased during the first 1 to 2 weeks of once-daily administration of therapeutic doses of omeprazole in parallel with inhibition of acid secretion. No further increase in serum gastrin occurred with continued treatment. In comparison with histamine H2-receptor antagonists, the median increases produced by 20 mg doses of omeprazole were higher (1.3 to 3.6 fold vs. 1.1 to 1.8 fold increase). Gastrin values returned to pretreatment levels, usually within 1 to 2 weeks after discontinuation of therapy.

Other Effects

Systemic effects of omeprazole in the CNS, cardiovascular and respiratory systems have not been found to date. Omeprazole, given in oral doses of 30 or 40 mg for 2 to 4 weeks, had no effect on thyroid function, carbohydrate metabolism, or circulating levels of parathyroid hormone, cortisol, estradiol, testosterone, prolactin, cholecystokinin or secretin.

No effect on gastric emptying of the solid and liquid components of a test meal was demonstrated after a single dose of omeprazole 90 mg. In healthy subjects, a single I.V. dose of omeprazole (0.35 mg/kg) had no effect on intrinsic factor secretion. No systematic dose-dependent effect has been observed on basal or stimulated pepsin output in humans. However, when intragastric pH is maintained at 4.0 or above, basal pepsin output is low, and pepsin activity is decreased.

As do other agents that elevate intragastric pH, omeprazole administered for 14 days in healthy subjects produced a significant increase in the intragastric concentrations of viable bacteria. The pattern of the bacterial species was unchanged from that commonly found in saliva. All changes resolved within three days of stopping treatment.

The course of Barrett's esophagus in 106 patients was evaluated in a U.S. double-blind controlled study of omeprazole 40 mg b.i.d. for 12 months followed by 20 mg b.i.d. for 12 months or ranitidine 300 mg b.i.d. for 24 months. No clinically significant impact on Barrett's mucosa by antisecretory therapy was observed. Although neosquamous epithelium developed during antisecretory therapy, complete elimination of Barrett's mucosa was not achieved. No significant difference was observed between treatment groups in development of dysplasia in Barrett's mucosa and no patient developed esophageal carcinoma during treatment. No significant differences between treatment groups were observed in development of ECL cell hyperplasia, corpus atrophic gastritis, corpus intestinal metaplasia, or colon polyps exceeding 3 mm in diameter.

12.3 Pharmacokinetics

Absorption

In separate in vivo bioavailability studies, when ZEGERID Oral Suspension and Capsules are administered on an empty stomach 1 hour prior to a meal, the absorption of omeprazole is rapid, with mean peak plasma levels (% CV) of omeprazole being 1954 ng/mL (33%) and 1526 ng/mL (49%), respectively, and time to peak of approximately 30 minutes (range 10-90 min) after a single-dose or repeated-dose administration. Absolute bioavailability of ZEGERID Powder for Oral Suspension (compared to I.V. administration) is about 30-40% at doses of 20 – 40 mg, due in large part to presystemic metabolism.

When ZEGERID Oral Suspension 40 mg/1680 mg was administered in a two-dose loading regimen, the omeprazole AUC (0-inf) (ng·hr/mL) was 1665 after Dose 1 and 3356 after Dose 2, while Tmax was approximately 30 minutes for both Dose 1 and Dose 2.

Following single or repeated once daily dosing, peak plasma concentrations of omeprazole from ZEGERID are approximately proportional from 20 to 40 mg doses, but a greater than linear mean AUC (three-fold increase) is observed when doubling the dose to 40 mg. The bioavailability of omeprazole from ZEGERID increases upon repeated administration.

When ZEGERID is administered 1 hour after a meal, the omeprazole AUC is reduced by approximately 24% relative to administration 1 hour prior to a meal.

Distribution

Omeprazole is bound to plasma proteins. Protein binding is approximately 95%.

Metabolism

Following single-dose oral administration of omeprazole, the majority of the dose (about 77%) is eliminated in urine as at least six metabolites. Two metabolites have been identified as hydroxyomeprazole and the corresponding carboxylic acid. The remainder of the dose was recoverable in feces. This implies a significant biliary excretion of the metabolites of omeprazole. Three metabolites have been identified in plasma – the sulfide and sulfone derivatives of omeprazole, and hydroxyomeprazole. These metabolites have very little or no antisecretory activity.

Excretion

Following single-dose oral administration of omeprazole, little if any, unchanged drug is excreted in urine. The mean plasma omeprazole half-life in healthy subjects is approximately 1 hour (range 0.4 to 3.2 hours) and the total body clearance is 500-600 mL/min.

Special Populations

Geriatric

The elimination rate of omeprazole was somewhat decreased in the elderly, and bioavailability was increased. Omeprazole was 76% bioavailable when a single 40-mg oral dose of omeprazole (buffered solution) was administered to healthy elderly subjects, versus 58% in young subjects given the same dose. Nearly 70% of the dose was recovered in urine as metabolites of omeprazole and no unchanged drug was detected. The plasma clearance of omeprazole was 250 mL/min (about half that of young subjects) and its plasma half-life averaged one hour, similar to that of young healthy subjects.

Pediatric

The pharmacokinetics of ZEGERID has not been studied in patients < 18 years of age.

Gender

There are no known differences in the absorption or excretion of omeprazole between males and females.

Hepatic Insufficiency

In patients with chronic hepatic disease, the bioavailability of omeprazole from a buffered solution increased to approximately 100% compared to an I.V. dose, reflecting decreased first-pass effect, and the mean plasma half-life of the drug increased to nearly 3 hours compared to the mean half-life of 1 hour in normal subjects. Plasma clearance averaged 70 mL/min, compared to a value of 500-600 mL/min in normal subjects. Dose reduction, particularly where maintenance of healing of erosive esophagitis is indicated, for the hepatically impaired should be considered.

Renal Insufficiency

In patients with chronic renal impairment, whose creatinine clearance ranged between 10 and 62 mL/min/1.73 m^2, the disposition of omeprazole from a buffered solution was very similar to that in healthy subjects, although there was a slight increase in bioavailability. Because urinary excretion is a primary route of excretion of omeprazole metabolites, their elimination slowed in proportion to the decreased creatinine clearance. No dose reduction is necessary in patients with renal impairment.

Asian Population

In pharmacokinetic studies of single 20-mg omeprazole doses, an increase in AUC of approximately four-fold was noted in Asian subjects compared to Caucasians. Dose adjustment, particularly where maintenance of healing of erosive esophagitis is indicated, for Asian subjects should be considered.

13 NONCLINICAL TOXICOLOGY

13.1 Carcinogenesis, Mutagenesis, Impairment of Fertility

In two 24-month carcinogenicity studies in rats, omeprazole at daily doses of 1.7, 3.4, 13.8, 44.0 and 140.8 mg/kg/day (approximately 0.35 to 28.5 times the human dose of 40 mg/day, based on body surface area) produced gastric ECL cell carcinoids in a dose-related manner in both male and female rats; the incidence of this effect was markedly higher in female rats, which had higher blood levels of omeprazole. Gastric carcinoids seldom occur in the untreated rat. In addition, ECL cell hyperplasia was present in all treated groups of both sexes. In one of these studies, female rats were treated with 13.8 mg omeprazole/kg/day (approximately 2.8 times the human dose of 40 mg/day, based on body surface area) for one year, then followed for an additional year without the drug. No carcinoids were seen in these rats. An increased incidence of treatment-related ECL cell hyperplasia was observed at the end of one year (94% treated versus 10% controls). By the second year the difference between treated and control rats was much smaller (46% versus 26%) but still showed more hyperplasia in the treated group. Gastric adenocarcinoma was seen in one rat (2%). No similar tumor was seen in male or female rats treated for two years. For this strain of rat no similar tumor has been noted historically, but a finding involving only one tumor is difficult to interpret. In a 52-week toxicity study in Sprague-Dawley rats, brain astrocytomas were found in a small number of males that received omeprazole at dose levels of 0.4, 2, and 16 mg/kg/day (about 0.1 to 3.3 times the human dose of 40 mg/day, based on body surface area). No astrocytomas were observed in female rats in this study. In a 2-year carcinogenicity study in Sprague-Dawley rats, no astrocytomas were found in males and females at the high dose of 140.8 mg/kg/day (about 28.5 times the human dose of 40 mg/day, based on body surface area). A 78-week mouse carcinogenicity study of omeprazole did not show increased tumor occurrence, but the study was not conclusive. A 26-week p53 (+/-) transgenic mouse carcinogenicity study was not positive.

Omeprazole was positive for clastogenic effects in an in vitro human lymphocyte chromosomal aberration assay, in one of two in vivo mouse micronucleus tests, and in an in vivo bone marrow cell chromosomal aberration assay. Omeprazole was negative in the in vitro Ames Test, an in vitro mouse lymphoma cell forward mutation assay and an in vivo rat liver DNA damage assay.

In 24-month carcinogenicity studies in rats, a dose-related significant increase in gastric carcinoid tumors and ECL cell hyperplasia was observed in both male and female animals [See Warnings and Precautions (5)]. Carcinoid tumors have also been observed in rats subjected to fundectomy or long-term treatment with other proton pump inhibitors or high doses of H2-receptor antagonists.

Omeprazole at oral doses up to 138 mg/kg/day (about 28 times the human dose of 40 mg/day, based on body surface area) was found to have no effect on the fertility and general reproductive performance in rats.

13.2 Animal Toxicology and/or Pharmacology

Reproductive Toxicology Studies

Reproduction studies conducted in pregnant rats at omeprazole doses up to 138 mg/kg/day (about 28 times the human dose of 40 mg/day, based on body surface area) and in pregnant rabbits at doses up to 69 mg/kg/day (about 28 times the human dose of 40 mg/day, based on body surface area) did not disclose any evidence for a teratogenic potential of omeprazole.

In rabbits, omeprazole in a dose range of 6.9 to 69 mg/kg/day (about 2.8 to 28 times the human dose of 40 mg/day, based on body surface area) produced dose-related increases in embryo-lethality, fetal resorptions and pregnancy disruptions. In rats, dose-related embryo/fetal toxicity and postnatal developmental toxicity were observed in offspring resulting from parents treated with omeprazole at 13.8 to 138.0 mg/kg/day (about 2.8 to 28 times the human dose of 40 mg/day, based on body surface area).

14 CLINICAL STUDIES

14.1 Duodenal Ulcer Disease

Active Duodenal Ulcer – In a multicenter, double-blind, placebo controlled study of 147 patients with endoscopically documented duodenal ulcer, the percentage of patients healed (per protocol) at 2 and 4 weeks was significantly higher with omeprazole 20 mg once a day than with placebo (p ≤ 0.01). (See Table 7)

Table 7: Treatment of Active Duodenal Ulcer % of Patients Healed
 | Omeprazole 20 mg a.m. (n = 99) | Placebo a.m. (n = 48)
Week 2 | 41* | 13
Week 4 | 75* | 27
* (p ≤ 0.01)

Complete daytime and nighttime pain relief occurred significantly faster (p ≤ 0.01) in patients treated with omeprazole 20 mg than in patients treated with placebo. At the end of the study, significantly more patients who had received omeprazole had complete relief of daytime pain (p ≤ 0.05) and nighttime pain (p ≤ 0.01).

In a multicenter, double-blind study of 293 patients with endoscopically documented duodenal ulcer, the percentage of patients healed (per protocol) at 4 weeks was significantly higher with omeprazole 20 mg once a day than with ranitidine 150 mg b.i.d. (p < 0.01). (See Table 8)

Table 8: Treatment of Active Duodenal Ulcer % of Patients Healed
 | Omeprazole 20 mg a.m. (n = 145) | Ranitidine 150 mg b.i.d. (n = 148)
Week 2 | 42 | 34
Week 4 | 82* | 63
* (p ≤ 0.01)

Healing occurred significantly faster in patients treated with omeprazole than in those treated with ranitidine 150 mg b.i.d. (p < 0.01).

In a foreign multinational randomized, double-blind study of 105 patients with endoscopically documented duodenal ulcer, 40 mg and 20 mg of omeprazole were compared to 150 mg b.i.d. of ranitidine at 2, 4 and 8 weeks. At 2 and 4 weeks both doses of omeprazole were statistically superior (per protocol) to ranitidine, but 40 mg was not superior to 20 mg of omeprazole, and at 8 weeks there was no significant difference between any of the active drugs. (See Table 9)

Table 9: Treatment of Active Duodenal Ulcer % of Patients Healed
 | Omeprazole |  | Ranitidine
 | 40 mg (n = 36) | 20 mg (n = 34) | 150 mg b.i.d. (n = 35)
Week 2 | 83* | 83* | 53
Week 4 | 100* | 97* | 82
Week 8 | 100 | 100 | 94
*(p ≤ 0.01)

14.2 Gastric Ulcer

In a U.S. multicenter, double-blind study of omeprazole 40 mg once a day, 20 mg once a day, and placebo in 520 patients with endoscopically diagnosed gastric ulcer, the following results were obtained. (See Table 10)

Table 10: Treatment of Gastric Ulcer % of Patients Healed (All Patients Treated)
 | Omeprazole 40 mg q.d. (n = 214) | Omeprazole 20 mg q.d. (n = 202) | Placebo (n = 104)
Week 4 | 55.6** | 47.5** | 30.8
Week 8 | 82.7**,+ | 74.8** | 48.1
** (p < 0.01) Omeprazole 40 mg or 20 mg versus placebo
^+ (p < 0.05) Omeprazole 40 mg versus 20 mg

For the stratified groups of patients with ulcer size less than or equal to 1 cm, no difference in healing rates between 40 mg and 20 mg was detected at either 4 or 8 weeks. For patients with ulcer size greater than 1 cm, 40 mg was significantly more effective than 20 mg at 8 weeks.

In a foreign, multinational, double-blind study of 602 patients with endoscopically diagnosed gastric ulcer, omeprazole 40 mg once a day, 20 mg once a day, and ranitidine 150 mg twice a day were evaluated. (See Table 11)

Table 11: Treatment of Gastric Ulcer % of Patients Healed (All Patients Treated)
 | Omeprazole 40 mg q.d. (n = 187) | Omeprazole 20 mg q.d. (n = 200) | Ranitidine 150 mg b.i.d. (n = 199)
Week 4 | 78.1**,++ | 63.5 | 56.3
Week 8 | 91.4**,++ | 81.5 | 78.4
**(p < 0.01) Omeprazole 40 mg versus ranitidine
^++(p < 0.01) Omeprazole 40 mg versus 20 mg

14.3 Gastroesophageal Reflux Disease (GERD)

Symptomatic GERD - A placebo controlled study was conducted in Scandinavia to compare the efficacy of omeprazole 20 mg or 10 mg once daily for up to 4 weeks in the treatment of heartburn and other symptoms in GERD patients without erosive esophagitis. Results are shown in Table 12.

Table 12: % Successful Symptomatic Outcomea
 | Omeprazole 20 mg a.m. | Omeprazole 10 mg a.m. | Placebo a.m.
All patients | 46*,† (n = 205) | 31† (n = 199) | 13 (n = 105)
Patients with confirmed GERD | 56*,† (n = 115) | 36† (n = 109) | 14 (n = 59)
a Defined as complete resolution of heartburn
* (p < 0.005) versus 10 mg
† (p < 0.005) versus placebo

Erosive Esophagitis - In a U.S. multicenter double-blind placebo controlled study of 40 mg or 20 mg of omeprazole delayed release capsules in patients with symptoms of GERD and endoscopically diagnosed erosive esophagitis of grade 2 or above, the percentage healing rates (per protocol) were as shown in Table 13.

Table 13: % Patients Healed
 | Omeprazole 40 mg (n = 87) | Omeprazole 20 mg (n = 83) | Placebo (n = 43)
Week 4 | 45* | 39* | 7
Week 8 | 75* | 74* | 14
* (p < 0.01) Omeprazole versus placebo.

In this study, the 40-mg dose was not superior to the 20-mg dose of omeprazole in the percentage healing rate. Other controlled clinical trials have also shown that omeprazole is effective in severe GERD. In comparisons with histamine H2-receptor antagonists in patients with erosive esophagitis, grade 2 or above, omeprazole in a dose of 20 mg was significantly more effective than the active controls. Complete daytime and nighttime heartburn relief occurred significantly faster (p < 0.01) in patients treated with omeprazole than in those taking placebo or histamine H2-receptor antagonists.

In this and five other controlled GERD studies, significantly more patients taking 20 mg omeprazole (84%) reported complete relief of GERD symptoms than patients receiving placebo (12%).

14.4 Long Term Maintenance Treatment of Erosive Esophagitis

In a U.S. double-blind, randomized, multicenter, placebo controlled study; two dose regimens of omeprazole were studied in patients with endoscopically confirmed healed esophagitis. Results to determine maintenance of healing of erosive esophagitis are shown in Table 14.

Table 14: Life Table Analysis
 | Omeprazole 20 mg q.d. (n = 138) | Omeprazole 20 mg 3 days per week (n = 137) | Placebo (n = 131)
Percent in endoscopic remission at 6 months | 70* | 34 | 11
* (p < 0.01) Omeprazole 20 mg once daily versus Omeprazole 20 mg 3 consecutive days per week or placebo.

In an international multicenter double-blind study, omeprazole 20 mg daily and 10 mg daily were compared to ranitidine 150 mg twice daily in patients with endoscopically confirmed healed esophagitis. Table 15 provides the results of this study for maintenance of healing of erosive esophagitis.

Table 15: Life Table Analysis
 | Omeprazole 20 mg q.d. (n = 131) | Omeprazole 10 mg q.d. (n = 133) | Ranitidine 150 mg b.i.d. (n = 128)
Percent in endoscopic remission at 12 months | 77* | 58‡ | 46
* (p = 0.01) Omeprazole 20 mg once daily versus Omeprazole 10 mg once daily or Ranitidine.
‡ (p = 0.03) Omeprazole 10 mg once daily versus Ranitidine.

In patients who initially had grades 3 or 4 erosive esophagitis, for maintenance after healing 20 mg daily of omeprazole was effective, while 10 mg did not demonstrate effectiveness.

14.5 Reduction of Risk of Upper Gastrointestinal Bleeding in Critically Ill Patients

A double-blind, multicenter, randomized, non-inferiority clinical trial was conducted to compare ZEGERID Oral Suspension 40 mg/1680 mg and I.V. cimetidine for the reduction of risk of upper gastrointestinal (GI) bleeding in critically ill patients (mean APACHE II score = 23.7). The primary endpoint was significant upper GI bleeding defined as bright red blood which did not clear after adjustment of the nasogastric tube and a 5 to 10 minute lavage, or persistent Gastroccult® positive coffee grounds for 8 consecutive hours which did not clear with 100 cc lavage. ZEGERID Oral Suspension 40 mg/1680 mg (two doses administered 6 to 8 hours apart on the first day via orogastric or nasogastric tube, followed by 40 mg q.d. thereafter) was compared to continuous I.V. cimetidine (300 mg bolus, and 50 to 100 mg/hr continuously thereafter) for up to 14 days (mean = 6.8 days). A total of 359 patients were studied, age range 16 to 91 (mean = 56 yrs), 58.5% were males, and 64% were Caucasians. The results of the study showed that ZEGERID was non-inferior to I.V. cimetidine, 10/181(5.5%) patients in the cimetidine group vs. 7/178 (3.9%) patients in the ZEGERID group experienced clinically significant upper GI bleeding.

15 REFERENCES

1. Friedman JM and Polifka JE. Omeprazole. In: Teratogenic Effects of Drugs. A Resource for Clinicians (TERIS). 2nd ed. Baltimore, MD: The Johns Hopkins University Press 2000; p. 516.
2. Kallen BAJ. Use of omeprazole during pregnancy – no hazard demonstrated in 955 infants exposed during pregnancy. Eur Obstet Gynecol Reprod Biol 2001; 96(1):63-8.
3. Ruigómez A, Rodriquez LUG, Cattaruzzi C, et al. Use of cimetidine, omeprazole, and ranitidine in pregnant women and pregnancy outcomes. Am J Epidemiol 1999; 150: 476-81.
4. Lalkin A, Loebstein, Addis A, et al. The safety of omeprazole during pregnancy: a multicenter prospective controlled study. Am J Obstet Gynecol 1998: 179:727-30.

16 HOW SUPPLIED/STORAGE AND HANDLING

ZEGERID 40-mg Capsules: Each opaque, hard gelatin, colored dark blue and white capsule, imprinted with the Santarus logo and “40”, contains 40 mg omeprazole and 1100 mg sodium bicarbonate.

NDC 54868-5611-0 Bottles of 30 capsules

Storage

Store at 25°C (77°F); excursions permitted to 15 - 30°C (59 - 86°F). [See USP Controlled Room Temperature].

Keep this medication out of the hands of children. Keep container tightly closed. Protect from light and moisture.

17 PATIENT COUNSELING INFORMATION

See FDA-Approved Patient Labeling.

Instruct patients that ZEGERID should be taken on an empty stomach at least one hour prior to a meal. [See Dosage and Administration (2)]

Instruct patients in Directions for Use as follows:

Capsules: Swallow intact capsule with water. DO NOT USE OTHER LIQUIDS. DO NOT OPEN CAPSULE AND SPRINKLE CONTENTS INTO FOOD.

Powder for Oral Suspension: Empty packet contents into a small cup containing 1-2 tablespoons of water. DO NOT USE OTHER LIQUIDS OR FOODS. Stir well and drink immediately. Refill cup with water and drink.

ZEGERID is available either as 40 mg or 20 mg capsules with 1100 mg sodium bicarbonate. ZEGERID is also available either as 40 mg or 20 mg single-dose packets of powder for oral suspension with 1680 mg sodium bicarbonate.

Patients should be instructed not to substitute Zegerid Capsules or Suspension for other ZEGERID dosage forms because different dosage forms contain different amounts of sodium bicarbonate and magnesium hydroxide. [See Dosage and Administration (2)]

Patients should be advised that since both the 20 mg and 40 mg oral suspension packets contain the same amount of sodium bicarbonate (1680 mg), two packets of 20 mg are not equivalent to one packet of ZEGERID 40 mg; therefore, two 20 mg packets of ZEGERID should not be substituted for one packet of ZEGERID 40 mg. Conversely ½ of a 40mg packet should not be substituted for one 20mg packet. [See Dosage and Administration (2)]

Patients should be advised that since both the 20 mg and 40 mg capsules contain the same amount of sodium bicarbonate (1100 mg), two capsules of 20 mg are not equivalent to one capsule of ZEGERID 40 mg; therefore, two 20 mg capsules of ZEGERID should not be substituted for one capsule of ZEGERID 40 mg. [See Dosage and Administration (2)]

Patients should be advised that this drug is not approved for use in patients less than 18 years of age. [See Pediatric Use (8.4)]

Patients on a sodium-restricted diet or patients at risk of developing congestive heart failure (CHF) should be informed of the sodium content of ZEGERID Capsules (304 mg per capsule) and ZEGERID Powder (460 mg per packet). Patients should be informed that chronic use of sodium bicarbonate may cause problems and increased sodium intake can cause swelling and weight gain. If this occurs, they should contact their healthcare provider. [See Warnings and Precautions (5.3)]

Patients should be informed that the most frequent adverse reactions associated with ZEGERID include headache, abdominal pain, nausea, diarrhea, vomiting and flatulence. [See Adverse Reactions (6)]

Pregnant women should be advised that a harmful effect of ZEGERID on the fetus can not be ruled out and that the drug should be used with caution during pregnancy. [See Pregnancy (8.1)]

Patients should be advised to use this drug with caution if they are regularly taking calcium supplements. [See Warnings and Precautions (5.3)]

Advise patients to immediately report and seek care for any cardiovascular or neurological symptoms including palpitations, dizziness, seizures and tetany as these may be signs of hypomagnesemia.[See Warnings and Precautions (5.5)]

SANTARUS ,INC.®

ZEGERID® Capsules are manufactured for Santarus, Inc., San Diego, CA 92130 by Norwich Pharmaceuticals, Inc., North Norwich, NY 13814.

ZEGERID® Powder for Oral Suspension is manufactured for Santarus, Inc. by Patheon Inc., Whitby, Ontario L1N 5Z5, Canada.

For more information call 1-888-778-0887

ZEGERID® is a registered trademark of Santarus, Inc.

© 2012 Santarus, Inc.

S0015H

Additional barcode labeling by:
Physicians Total Care, Inc.
Tulsa, Oklahoma 74146

FDA-APPROVED PATIENT LABELING

ZEGERID (ze' ger id)
(omeprazole / sodium bicarbonate)
Powder for Oral Suspension and Capsules

Read the Patient Information that comes with ZEGERID before you start taking it and each time you get a refill. There may be new information. This leaflet does not take the place of talking to your healthcare provider about your medical condition or treatment.

What is ZEGERID?

ZEGERID is a medicine called a proton pump inhibitor (PPI). ZEGERID reduces the amount of acid in your stomach.

ZEGERID is used in adults for:

- for 4 weeks to heal ulcers in the first part of the small bowel (duodenal ulcers). Your doctor may prescribe an additional 4 weeks of ZEGERID.
- for up to 8 weeks for healing stomach ulcers
- for up to 4 weeks to treat heartburn and other symptoms that happen with gastroesophageal reflux disease (GERD).
  GERD is a chronic condition (lasts a long time) that occurs when acid from the stomach backs up into the esophagus (food pipe) causing symptoms, such as heartburn, or damage to the lining of the esophagus. Common symptoms include frequent heartburn that will not go away, a sour or bitter taste in the mouth, and difficulty swallowing.
- for up to 8 weeks to heal acid-related damage to the lining of the esophagus (called erosive esophagitis or EE)
- to maintain healing of the esophagus. ZEGERID has not been studied for treatment lasting longer than 12 months (1 year)
- to lower the risk of stomach bleeding in critically ill patients (40 mg Oral Suspension Only)

It is not known if ZEGERID is safe and effective in children and adolescents less than 18 years of age.

ZEGERID may help your acid-related symptoms, but you could still have serious stomach problems. Talk with your doctor.

Who should not take ZEGERID?

Do not take ZEGERID if you:

- are allergic to any of the ingredients in ZEGERID. See the end of this leaflet for a complete list of ingredients in ZEGERID.
- are allergic to any other PPI medicine.

What should I tell my doctor before I take ZEGERID?

Before you take ZEGERID, tell your doctor if you:

- have been told that you have low magnesium levels in your blood.
- have any liver problems.
- have heart failure.
- have Bartter's syndrome (a rare kidney disorder).
- have any allergies.
- are pregnant or planning to become pregnant. It is not known if ZEGERID can harm your unborn baby. Talk to your doctor if you are pregnant or plan to become pregnant.
- are breastfeeding or planning to breastfeed. You and your doctor should decide if you will take ZEGERID or breastfeed. You should not do both. Sodium bicarbonate (a part of ZEGERID) should be used with caution in nursing mothers.

Tell your doctor about all the medicines you take, including prescription and non-prescription medicines, vitamins and herbal supplements. ZEGERID may affect how other medicines work, and other medicines may affect how ZEGERID works. This can cause serious side effects. Know the medicines that you take. Keep a list of them with you and show it to your doctor when you get a new medicine. Be sure to tell your doctor if you are taking:

- diazepam (Valium)®
- warfarin (Coumadin)®
- phenytoin (Dilantin)®
- cyclosporine
- disulfiram (Antabuse)®
- benzodiazepines
- ketoconazole (Nizoral)®
- ampicillin sodium (Unazyn)® or ampicillin trihydrate (Principen)®
- iron salts
- digoxin
- voriconazole (Nizoral)®
- atazanavir (Reyataz)®
- nelfinavir (Viracept)®
- tacrolimus (Prograf)®
- saquinavir (Fortovase)®
- clarithromycin
- clopidogrel (Plavix)
- Methotrexate

How should I take ZEGERID?

- Take ZEGERID exactly as prescribed by your doctor. Do not change your dose or stop taking ZEGERID without talking to your doctor. Take ZEGERID for as long as it is prescribed even if you feel better.
- Take ZEGERID on an empty stomach at least one hour before a meal.
- Empty the contents of a packet of ZEGERID Powder for Oral Suspension into a small cup containing 1-2 tablespoons of water. DO NOT USE OTHER LIQUIDS OR FOODS. Stir well and drink immediately. Refill cup with water and drink.
- Swallow ZEGERID Capsules whole with water. DO NOT USE OTHER LIQUIDS. Do not crush or chew the capsule. Do not open the capsule and sprinkle contents into food.
- If you forget to take a dose of ZEGERID, take it as soon as you remember. If it is almost time for your next dose, do not take the missed dose. Take the next dose at your regular time. Do not take two doses to make up for a missed dose.
- Do not substitute two 20 mg packets for one 40 mg packet of ZEGERID Powder for Oral Suspension because you will receive twice the amount of sodium bicarbonate. Talk to your doctor if you have questions.
- Do not substitute two 20 mg capsules for one 40 mg capsule of ZEGERID because you will receive twice the amount of sodium bicarbonate. Talk to your doctor if you have questions.
- If you take too much ZEGERID, call your doctor or Poison Control Center right away, or go to the emergency room.
- Your doctor may prescribe antibiotic medicines with ZEGERID to help treat a stomach infection and heal stomach-area (duodenal) ulcers that are caused by bacteria called H. pylori. Make sure you read the patient information that comes with an antibiotic before you start taking it.
- See the “Patient Instructions for Use” at the end of this leaflet for instructions on how to mix and give ZEGERID Powder for Oral Suspension through a nasogastric tube or orogastric tube.

What are the possible side effects of ZEGERID?

ZEGERID may cause serious allergic reactions. See the end of this leaflet for a complete list of ingredients in ZEGERID.

- Serious allergic reactions. Tell your doctor if you get any of the following symptoms with ZEGERID.
- rash
- face swelling
- throat tightness
- difficulty breathing

Your doctor may stop ZEGERID if these symptoms happen.

- Low magnesium levels in your body. This problem can be serious. Low magnesium can happen in some people who take a proton pump inhibitor medicine for at least 3 months. If low magnesium levels happen, it is usually after a year of treatment. You may or may not have symptoms of low magnesium.

Tell your doctor right away if you have any of these symptoms:

  - seizures
  - dizziness
  - abnormal or fast heart beat
  - jitteriness
  - jerking movements or shaking (tremors)
  - muscle weakness
  - spasms of the hands and feet
  - cramps or muscle aches
  - spasm of the voice box

Your doctor may check the level of magnesium in your body before you start taking ZEGERID, or during treatment if you will be taking ZEGERID for a long period of time.

The most common side effects with ZEGERID include:

- headache
- abdominal pain
- nausea
- diarrhea
- vomiting
- gas

Using ZEGERID for a long time may cause problems like swelling and weight gain. Tell your doctor if this happens..

If you are on a low-sodium diet or at risk of developing congestive heart failure (CHF), you and your doctor should decide if you will take ZEGERID.

People who are taking multiple daily doses of proton pump inhibitor medicines for a long period of time may have an increased risk of fractures of the hip, wrist or spine.

Tell your doctor about any side effects that bother you or that do not go away. These are not all the possible side effects of ZEGERID. For more information, ask your doctor or pharmacist. Call your doctor for medical advice about side effects. You may report side effects to the FDA at 1-800-FDA-1088

How should I store ZEGERID?

- Store ZEGERID in a dry place at room temperature, 59 °F to 86 °F (15 °C to 30 °C).

Keep ZEGERID and all medicines out of the reach of children.

General Information about ZEGERID

Medicines are sometimes prescribed for conditions other than those described in patient information leaflets. Do not use ZEGERID for any condition for which it was not prescribed by your doctor. Do not give ZEGERID to other people, even if they have the same symptoms as you. It may harm them.

This leaflet summarizes the most important information about ZEGERID. If you would like more information, talk to your doctor. You can also ask your doctor or pharmacist for information about ZEGERID that is written for healthcare professionals. For full product information, visit the website at http://www.santarus.com or call the toll-free number 1-888-778-0887.

Patient Instructions for Use

For instructions on taking ZEGERID Capsules and ZEGERID Powder for Oral Suspension by mouth, please see “ How Should I Take ZEGERID? ”

For giving ZEGERID Powder for Oral Suspension through a nasogastric tube (NG tube) or orogastric tube, as prescribed by your doctor. Follow the instructions below:

- Add 20 mL of water to a catheter tipped syringe and then add the contents of a packet as instructed by your doctor. Use only a catheter tipped syringe to give ZEGERID through a NG tube or orogastric tube.
- Shake the syringe to dissolve the powder.
- Give the medicine through the NG or orogastric tube into the stomach right away.
- Refill the syringe with an equal amount of water.
- Shake and flush any remaining contents from the NG tube or orogastric tube into the stomach.

What are the ingredients in ZEGERID?

Active Ingredients: omeprazole / sodium bicarbonate

Inactive ingredients of ZEGERID Powder for Oral Suspension: xylitol, sucrose, sucralose, xanthan gum, and flavorings.
Inactive ingredients of ZEGERID Capsules: croscarmellose sodium and sodium stearyl fumarate.

For prescription only

Revised April 2012

ZEGERID® is a registered trademark of Santarus, Inc.

ZEGERID® Capsules are manufactured for Santarus, Inc., San Diego, CA 92130 by Norwich Pharmaceuticals, Inc., North Norwich, NY 13814.

ZEGERID® Powder for Oral Suspension is manufactured for Santarus, Inc. by Patheon Inc., Whitby, Ontario L1N 5Z5, Canada.

For more information call 1-888-778-0887

© 2012 Santarus, Inc.

PACKAGE LABEL - PRINCIPAL DISPLAY PANEL – 40 MG LABEL

NDC 54868-5611-0

ZEGERID®

(omeprazole/sodium bicarbonate)

Capsules

30 Capsules

Rx only

40mg/1100mg